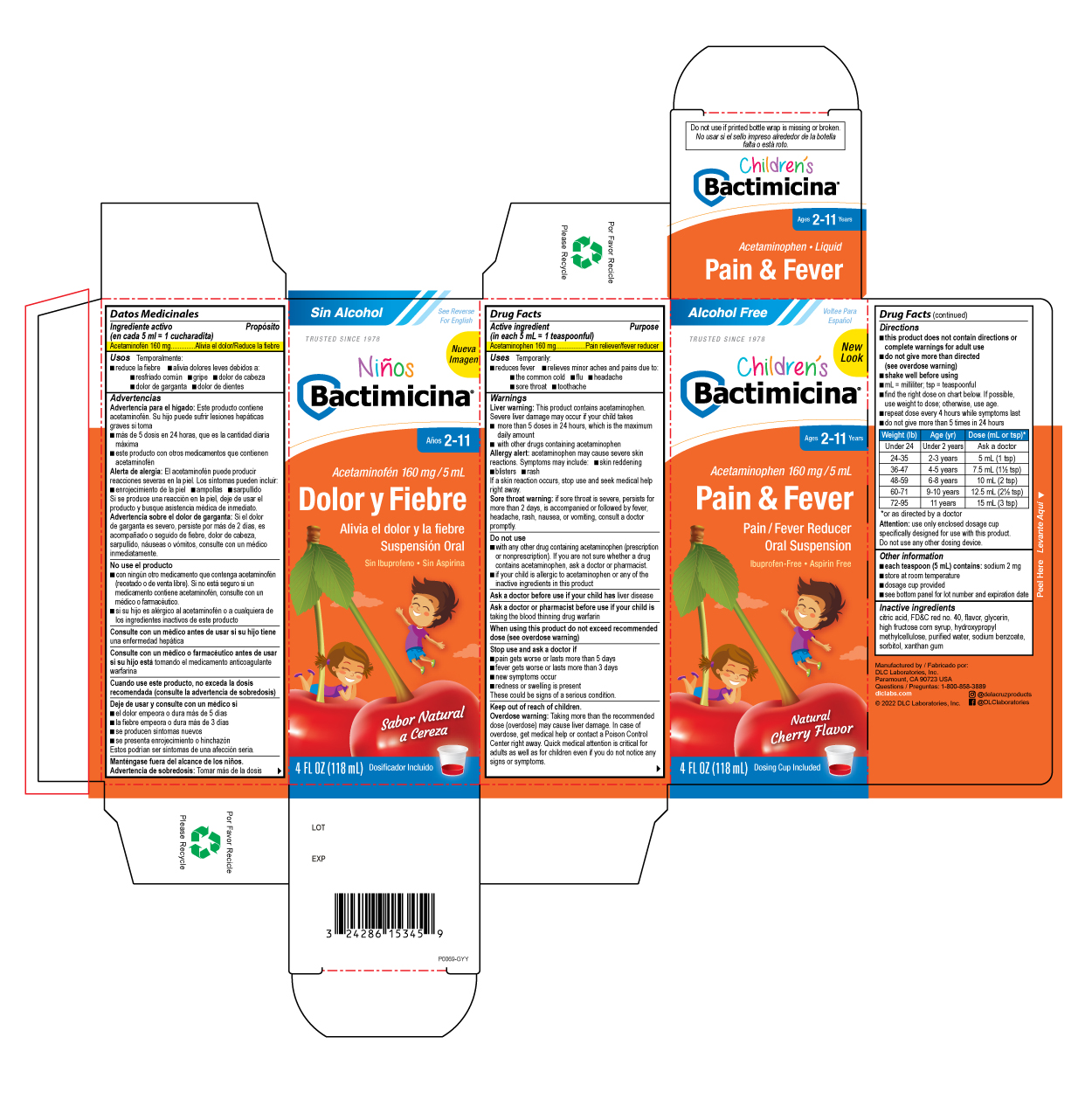 DRUG LABEL: Bactimicina Childrens Pain and Fever
NDC: 24286-1550 | Form: LIQUID
Manufacturer: DLC Laboratories, Inc.
Category: otc | Type: HUMAN OTC DRUG LABEL
Date: 20260107

ACTIVE INGREDIENTS: ACETAMINOPHEN 160 mg/5 mL
INACTIVE INGREDIENTS: FD&C RED NO. 40; CORN SYRUP; HYPROMELLOSE, UNSPECIFIED; WATER; CITRIC ACID MONOHYDRATE; SODIUM BENZOATE; SORBITOL; GLYCERIN; XANTHAN GUM

BACTIMICINA®CHILDREN'S PAIN AND FEVER

Drug Facts

Active ingredient (in each 5 mL = 1 teaspoonful)

Acetaminophen 160 mg

Purpose

Pain reliever/fever reducer

Uses

Temporarily:

- reduces fever
- relieves minor aches and pains due to:
  - the common cold
  - flu
  - headache
  - sore throat
  - toothache

Warnings

Liver warning

This product contains acetaminophen. Severe liver damage may occur if your child takes

- more than 5 doses in 24 hours, which is the maximum daily amount
- with other drugs containing acetaminophen

Allergy alert:acetaminophen may cause severe skin reactions. Symptoms may include:

- skin reddening
- blisters
- rash

If a skin reaction occurs, stop use and seek medical help right away.

Sore throat warning:if sore throat is severe, persists for more than 2 days, is accompanied or followed by fever, headache, rash, nausea, or vomiting, consult a doctor promptly.

Do not use

- with any other drug containing acetaminophen (prescription or nonprescription). If you are not sure whether a drug contains acetaminophen, ask a doctor or pharmacist.
- if your child is allergic to acetaminophen or any of the inactive ingredients in this product

Ask a doctor before use if your child hasliver disease

Ask a doctor or pharmacist before use if your child istaking the blood thinning drug warfarin

When using this product do not exceed recommended dose (see overdose warning)

Stop use and ask a doctor if

- pain gets worse or lasts more than 5 days
- fever gets worse or lasts more than 3 days
- new symptoms occur
- redness or swelling is present

These could be signs of a serious condition.

Keep out of reach of children.

Overdose warning

Taking more than the recommended dose (overdose) may cause liver damage. In case of overdose, get medical help or contact a Poison Control Center right away. Quick medical attention is critical for adults as well as for children even if you do not notice any signs or symptoms.

Directions

- this product does not contain directions or complete warnings for adult use
- do not give more than directed (see overdose warning)
- shake well before using
- mL = milliliter; tsp = teaspoonful
- find the right dose on chart below. If possible, use weight to dose; otherwise, use age.
- repeat dose every 4 hours while symptoms last
- do not give more than 5 times in 24 hours

Weight (lb) | Age (yr) | Dose (mL or tsp) [or as directed by a doctor]
Under 24 | Under 2 years | Ask a doctor
24-35 | 2-3 years | 5 mL (1 tsp)
36-47 | 4-5 years | 7.5 mL (1½ tsp)
48-59 | 6-8 years | 10 mL (2 tsp)
60-71 | 9-10 years | 12.5 mL (2½ tsp)
72-95 | 11 years | 15 mL (3 tsp)

Attention:use only enclosed dosage cup specifically designed for use with this product. Do not use any other dosing device.

Other information

- each teaspoon (5 mL) contains:sodium 2 mg
- store at room temperature
- dosage cup provided
- do not use if printed bottle wrap is missing or broken
- see bottom panel for lot number and expiration date

Inactive ingredients

citric acid, FD&C red no. 40, flavor, glycerin, high fructose corn syrup, hydroxypropyl methycellulose, purified water, sodium benzoate, sorbitol, xanthan gum

Questions

1-800-858-3889

Manufactured by
DLC Laboratories, Inc.
Paramount, CA 90723 USA

PRINCIPAL DISPLAY PANEL - 118 mL Bottle Label

Alcohol Free

Voltee Para

Español

TRUSTED SINCE 1978

New Look

Children's

Bactimicina®

Ages 2-11 Years

Acetaminophen 160 mg/5 mL

Pain & Fever

Pain/Fever Reducer

Oral Suspension

Ibuprofen-Free • Asprin Free

Natural

Cherry Flavor

4 FL OZ (118 mL) Dosing Cup Included